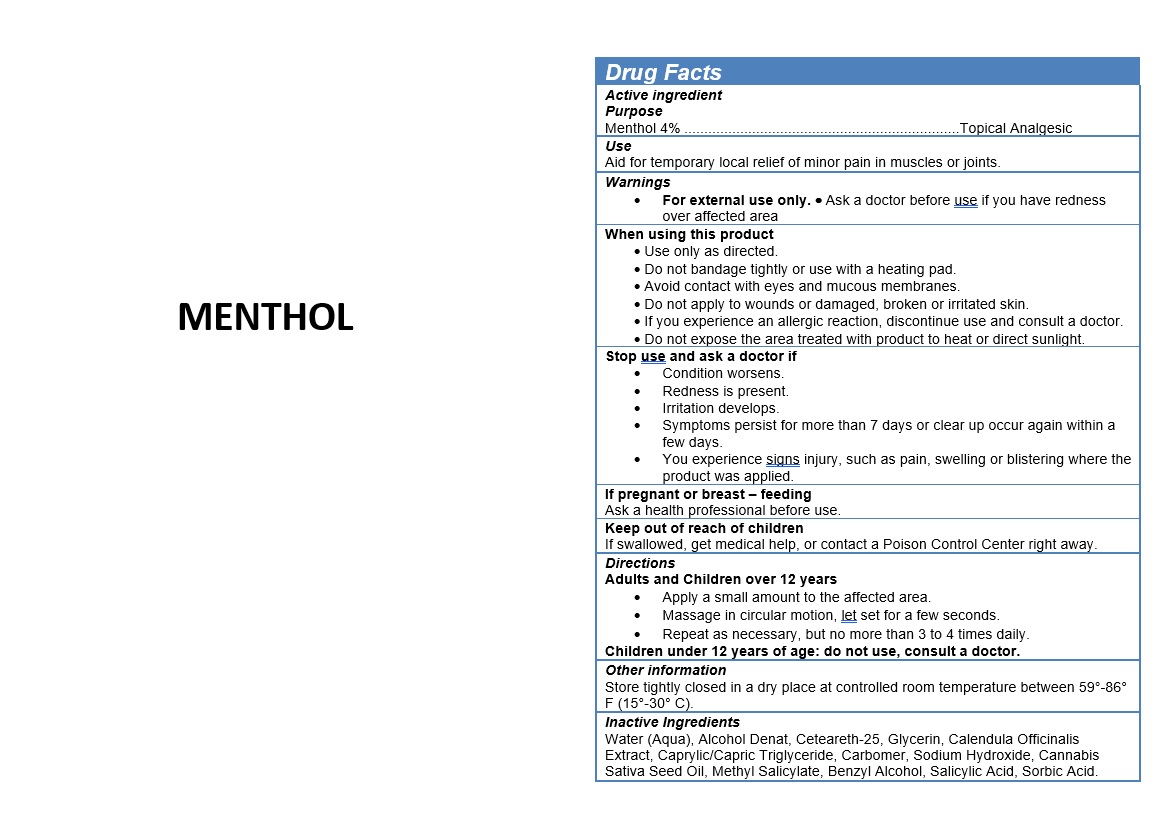 DRUG LABEL: MENTHOL
NDC: 49283-577 | Form: GEL
Manufacturer: CHEMCO CORPORATIOM
Category: otc | Type: HUMAN OTC DRUG LABEL
Date: 20251230

ACTIVE INGREDIENTS: MENTHOL, UNSPECIFIED FORM 4 g/100 mL
INACTIVE INGREDIENTS: CETEARETH-25; MEDIUM-CHAIN TRIGLYCERIDES; GLYCERIN; ALCOHOL; SALICYLIC ACID; CARBOMER 940; SORBIC ACID; SODIUM HYDROXIDE; BENZYL ALCOHOL; CALENDULA OFFICINALIS FLOWER; METHYL SALICYLATE; CANNABIS SATIVA SEED OIL

49283-577-03

ACTIVE INGREDIENT

Menthol 4%

PURPOSE

Topical Analgesic

USE

Aid for temporary local relief of minor pain in muscles or joints.

WARNINGS

For external use only. · Ask a doctor before use if you have redness over affected area

WHEN USING

Use only as directed.
Do not bandage tightly or use with a heating pad.
Avoid contact with eyes and mucous membranes.
Do not apply to wounds or damaged, broken or irritated skin.
If you experience an allergic reaction, discontinue use and consult a doctor.

Do not expose the area treated with product to heat or direct sunlight.

Stop use and ask a doctor if

Condition worsens.
Redness is present.
Irritation develops.
Symptoms persist for more than 7 days or clear up occur again within a few days.

You experience signs injury, such as pain, swelling or blistering where the product was applied.

PREGNANCY OR BREAST FEEDING

Ask a health professional before use.

KEEP OUT OF REACH OF CHILDREN

If swallowed, get medical help, or contact a Poison Control Center right away.

DIRECTIONS

Adults and Children over 12 years

Apply a small amount to the affected area.
Massage in circular motion, let set for a few seconds.
Repeat as necessary, but no more than 3 to 4 times daily.

Children under 12 years of age: do not use, consult a doctor.

OTHER SAFETY INFORMATION

Store tightly closed in a dry place at controlled room temperature between 59°-86° F (15°-30° C).

INACTIVE INGREDIENT

Water (Aqua), Alcohol Denat, Ceteareth-25, Glycerin, Calendula Officinalis Extract, Caprylic/Capric Triglyceride, Carbomer, Sodium Hydroxide, Cannabis Sativa Seed Oil, Methyl Salicylate, Benzyl Alcohol, Salicylic Acid, Sorbic Acid.